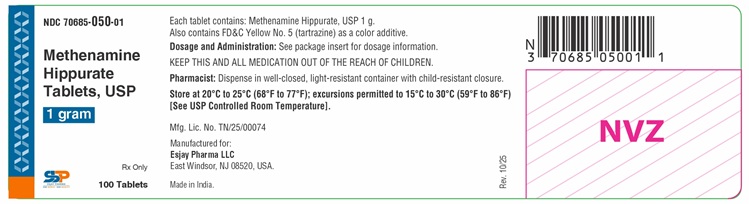 DRUG LABEL: Methenamine Hippurate
NDC: 70685-050 | Form: TABLET
Manufacturer: Esjay Pharma LLC
Category: prescription | Type: Human Prescription Drug Label
Date: 20251024

ACTIVE INGREDIENTS: METHENAMINE HIPPURATE 1 g/1 1
INACTIVE INGREDIENTS: FD&C YELLOW NO. 5; MAGNESIUM STEARATE; POVIDONE; SACCHARIN SODIUM

Methenamine Hippurate Tablets USP
Rx only

.

To reduce the development of drug-resistant bacteria and maintain the effectiveness of methenamine hippurate tablets and other antibacterial drugs, methenamine hippurate tablets should be used only to treat or prevent infections that are proven or strongly suspected to be caused by bacteria.

DESCRIPTION

Each yellow, capsule-shaped tablet contains 1 g Methenamine Hippurate, USP which is the hippuric acid salt of methenamine (hexamethylene tetramine). The tablet also contains inactive ingredients: FD&C Yellow No. 5 (tartrazine, see PRECAUTIONS), magnesium stearate, povidone, and saccharin sodium.

ACTIONS
Microbiology: Methenamine hippurate tablets have antibacterial activity because the methenamine component is hydrolyzed to formaldehyde in acid urine. Hippuric acid, the other component, has some antibacterial activity and also acts to keep the urine acid. The drug is generally active against E. coli, enterococci and staphylococci. Enterobacter aerogenes is generally resistant. The urine must be kept sufficiently acid for urea-splitting organisms such as Proteus and Pseudomonas to be inhibited.

Human Pharmacology: Within 1/2 hour after ingestion of a single 1-gram dose of methenamine hippurate tablets, antibacterial activity is demonstrable in the urine. Urine has continuous antibacterial activity when methenamine hippurate tablets are administered at the recommended dosage schedule of 1-gram twice daily. Over 90% of methenamine moiety is excreted in the urine within 24 hours after administration of a single 1-gram dose. Similarly, the hippurate moiety is rapidly absorbed and excreted, and it reaches the urine by both tubular secretion and glomerular filtration. This action may be important in older patients or in those with some degree of renal impairment.

INDICATIONS

Methenamine hippurate tablets are indicated for prophylactic or suppressive treatment of frequently recurring urinary tract infections when long-term therapy is considered necessary. This drug should only be used after eradication of the infection by other appropriate antimicrobial agents.

To reduce the development of drug-resistant bacteria and maintain the effectiveness of methenamine hippurate tablets and other antibacterial drugs, methenamine hippurate tablets should be used only to treat or prevent infections that are proven or strongly suspected to be caused by susceptible bacteria. When culture and susceptibility information are available, they should be considered in selecting or modifying antibacterial therapy. In the absence of such data, local epidemiology and susceptibility patterns may contribute to the empiric selection of therapy.

CONTRAINDICATIONS

Methenamine hippurate tablets are contraindicated in patients with renal insufficiency, severe hepatic insufficiency, or severe dehydration. Methenamine preparations should not be given to patients taking sulfonamides because some sulfonamides may form an insoluble precipitate with formaldehyde in the urine.

WARNING

Large doses of methenamine (8 grams daily for 3 to 4 weeks) have caused bladder irritation, painful and frequent micturition, albuminuria, and gross hematuria.

PRECAUTIONS

Prescribing methenamine hippurate tablets in the absence of a proven or strongly suspected bacterial infection or a prophylactic indication is unlikely to provide benefit to the patient and increases the risk of the development of drug-resistant bacteria.

1. Care should be taken to maintain an acid pH of the urine, especially when treating infections due to urea-splitting organisms such as Proteus and strains of Pseudomonas.
2. In a few instances in one study, the serum transaminase levels were slightly elevated during treatment but returned to normal while the patients were still taking methenamine hippurate tablets. Because of this report, it is recommended that liver function studies be performed periodically on patients taking the drug, especially those with liver dysfunction.
3. Use in Pregnancy: In early pregnancy the safe use of methenamine hippurate tablets is not established. In the last trimester, safety is suggested, but not definitely proved. No adverse effects on the fetus were seen in studies in pregnant rats and rabbits.
Methenamine hippurate tablets taken during pregnancy can interfere with laboratory tests of urine estriol (resulting in unmeasurably low values) when acid hydrolysis is used in the laboratory procedure. This interference is due to the presence in the urine of methenamine and/or formaldehyde. Enzymatic hydrolysis, in place of acid hydrolysis, will circumvent this problem.
4. This product contains FD&C Yellow No. 5 (tartrazine), which may cause allergic-type reactions (including bronchial asthma) in certain susceptible individuals. Although the overall incidence of FD&C Yellow No. 5 (tartrazine) sensitivity in the general population is low, it is frequently seen in patients who also have aspirin hypersensitivity.

Geriatric Use
Clinical studies of methenamine hippurate tablets did not include sufficient numbers of subjects aged 65 and over to determine whether they respond differently from younger subjects. Other reported clinical experience has not identified differences in responses between the elderly and younger patients. In general, dose selection for an elderly patient should be cautious, usually starting at the low end of the dosing range, reflecting the greater frequency of decreased hepatic, renal or cardiac function, and of concomitant disease or other drug therapy.

Methenamine hippurate tablets are contraindicated in patients with renal insufficiency and severe hepatic insufficiency (see CONTRAINDICATIONS).

Information for Patients
Patients should be counseled that antibacterial drugs including methenamine hippurate tablets should only be used to treat bacterial infections. They do not treat viral infections (e.g., the common cold). When methenamine hippurate tablets are prescribed to treat a bacterial infection, patients should be told that although it is common to feel better early in the course of therapy, the medication should be taken exactly as directed. Skipping doses or not completing the full course of therapy may (1) decrease the effectiveness of the immediate treatment and (2) increase the likelihood that bacteria will develop resistance and will not be treatable by methenamine hippurate tablets or other antibacterial drugs in the future.

ADVERSE REACTIONS

Minor adverse reactions have been reported in less than 3.5% of patients treated. These reactions have included nausea, upset stomach, dysuria, and rash.

To report SUSPECTED ADVERSE REACTIONS, contact Esjay Pharma LLC at 1-800-239-9339 or FDA at 1-800-FDA-1088 or www.fda.gov/medwatch.

DOSAGE AND ADMINISTRATION

1 tablet (1.0 g) twice daily (morning and night) for adults and pediatric patients over 12 years of age. 1/2 to 1 tablet (0.5 to 1.0 g) twice daily (morning and night) for pediatric patients 6 to 12 years of age. Since the antibacterial activity of methenamine hippurate tablets is greater in acid urine, restriction of alkalinizing foods and medications is desirable. If necessary, as indicated by urinary pH and clinical response, supplemental acidification of the urine should be instituted. The efficacy of therapy should be monitored by repeated urine cultures.

HOW SUPPLIED

1 gram - Yellow, capsule shaped tablet debossed with E50 on one side and scored on other side, available in bottles of 100 (NDC 70685-050-01).

Store at 20°C to 25°C (68°F to 77°F); excursions permitted to 15°C to 30°C (59°F to 86°F) [See USP Controlled Room Temperature].

Dispense in well-closed, light-resistant container with child-resistant closure.

Manufactured for:
Esjay Pharma LLC
East Windsor, NJ 08520, USA.

Made in India

Rev. 10/2025

PACKAGE LABEL.PRINCIPAL DISPLAY PANEL

Container Label (100s)